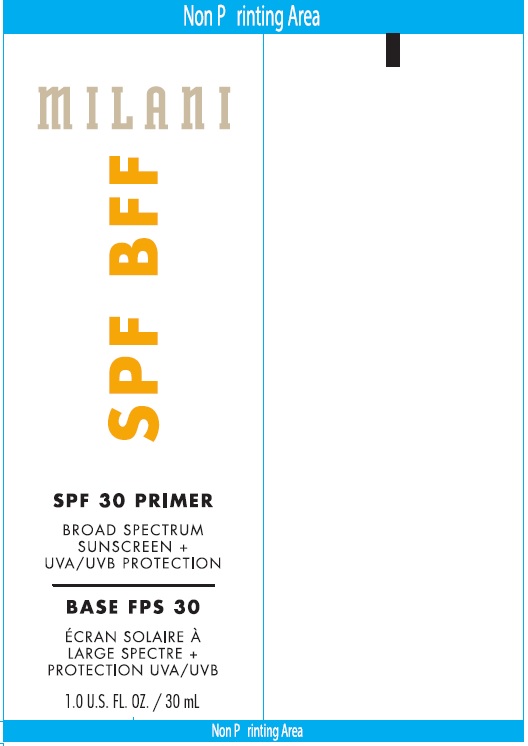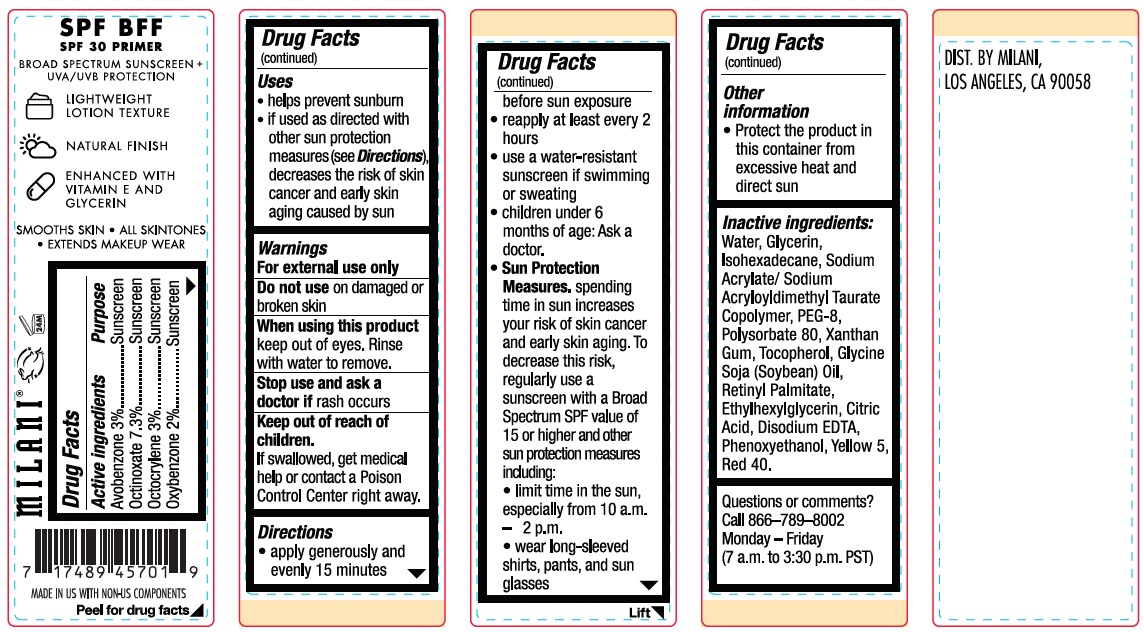 DRUG LABEL: Milani SPF BFF 30 Primer
NDC: 71435-0001 | Form: CREAM
Manufacturer: New Milani Group, LLC
Category: otc | Type: HUMAN OTC DRUG LABEL
Date: 20231212

ACTIVE INGREDIENTS: AVOBENZONE 30 mg/1 mL; OCTINOXATE 73 mg/1 mL; OCTOCRYLENE 30 mg/1 mL; OXYBENZONE 20 mg/1 mL
INACTIVE INGREDIENTS: WATER; GLYCERIN; ISOHEXADECANE; SODIUM ACRYLATE; SODIUM ACRYLOYLDIMETHYLTAURATE; POLYETHYLENE GLYCOL 400; POLYSORBATE 80; XANTHAN GUM; TOCOPHEROL; SOYBEAN OIL; VITAMIN A PALMITATE; ETHYLHEXYLGLYCERIN; CITRIC ACID MONOHYDRATE; EDETATE DISODIUM ANHYDROUS; PHENOXYETHANOL; FD&C YELLOW NO. 5; FD&C RED NO. 40

Milani SPF BFF 30 Primer

Active ingredients

Avobenzone 3%, Octinoxate 7.3% Octocrylene 3% Oxybenzone 2%

Purpose

Sunscreen

Uses

- helps prevent sunburn
- if used as directed with other sun protection measures (see), decreases the risk of skin cancer and early skin aging caused by the sun Directions

Warnings

For external use only

Do not use

on damaged or broken skin

When using this product

keep out of eyes. Rinse with water to remove.

Stop use and ask a doctor if

rash occurs

Keep out of reach of children.

If swallowed, get medical help or contact a Poison Control Center right away.

Directions

- apply generously and evenly 15 minutes before sun exposure
- reapply at least every 2 hours
- use a water-resistant sunscreen if swimming or sweating
- children under 6 months of age: Ask a doctor.
- spending time in the sun increases your risk of skin cancer and early skin aging. To decrease this risk, regularly use a sunscreen with a Broad Spectrum SPF value of 15 or higher and other sun protection measures including: Sun Protection Measures.
- limit time in the sun, especially from 10 a.m.-2 p.m.
- wear long-sleeved shirts, pants, and sunglasses

Other information

- Protect the product in this container from excessive heat and direct sun

Inactive ingredients:

Water, Glycerin, Isohexadecane, Sodium Acrylate/ Sodium Acryloyldimethyl Taurate Copolymer, PEG-8, Polysorbate 80, Xanthan Gum, Tocopherol, Glycine Soja (Soybean) Oil, Retinyl Palmitate, Ethylhexylglycerin, Citric Acid, Disodium EDTA, Phenoxyethanol, Yellow 5, Red 40.

Questions or comments?

Call 866-789-8002 Monday - Friday (7 a.m. to 3:30 p.m. PST)